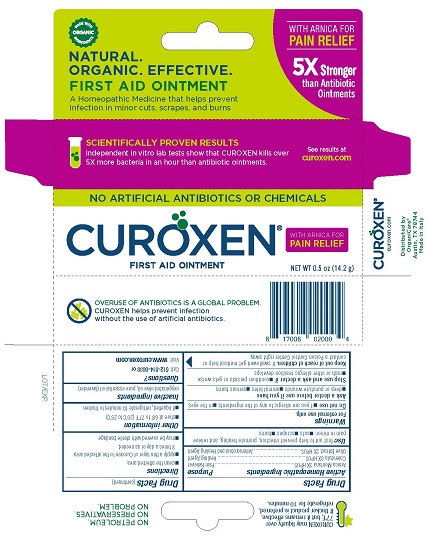 DRUG LABEL: Curoxen Pain Relief
NDC: 71042-002 | Form: OINTMENT
Manufacturer: OrganiCare Nature's Science, LLC
Category: homeopathic | Type: HUMAN OTC DRUG LABEL
Date: 20241212

ACTIVE INGREDIENTS: ARNICA MONTANA 3 [hp_X]/14 g; OLEA EUROPAEA FRUIT VOLATILE OIL 2 [hp_X]/14 g; CALENDULA OFFICINALIS FLOWERING TOP 3 [hp_X]/14 g
INACTIVE INGREDIENTS: LAVENDER OIL; OLIVE OIL

CUROXEN FIRST AID OINTMENT WITH ARNICA

Drug Facts

Active Homeopathic Ingredients

Arnica Montana 3X HPUS

Calendula 3X HPUS

Olive Extract 2X HPUS

Purpose

Pain Reliever

Healing Agent

Antimicrobial and Healing Agent

Use

first aid to help prevent infection, promote healing, and relieve pain in minor:

- cuts
- scrapes
- burns

Warnings

For external use only.

Do not use

- if you are allergic to any of the ingredients
- in the eyes

Ask a doctor before use if you have

- deep or puncture wounds
- animal bites
- serious burns

Stop use and ask a doctor if

- condition persists or gets worse
- rash or other allergic reaction develops

Keep out of reach of children. If swallowed get medical help or contact a Poison Control Center right away.

Directions

- clean the affected area
- apply a thin layer of Curoxen to the affected area 3 times a day or as needed
- may be covered with a sterile bandage

Other information

- store at 68° to 77°F (20° to 25°C)
- if liquefied, refrigerate 10 minutes to thicken

Inactive ingredients

oxygenated olive oil, pure essential oil (lavender)

Questions?

Call 512-814-0038 or

Visit www.curoxen.com

Distributed by

OrganiCare®

Austin, TX 78744

Made in Italy

PACKAGE LABEL

CUROXEN®

WITH ARNICA FOR PAIN RELIEF

FIRST AID OINTMENT

A Homeopathic Medicine that helps prevent Infection in minor cuts, scrapes, and burns

NET WT 0.5 oz (14.2 g)